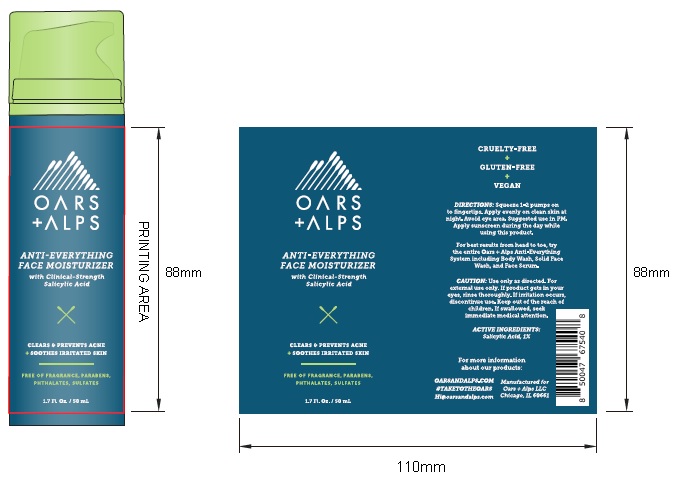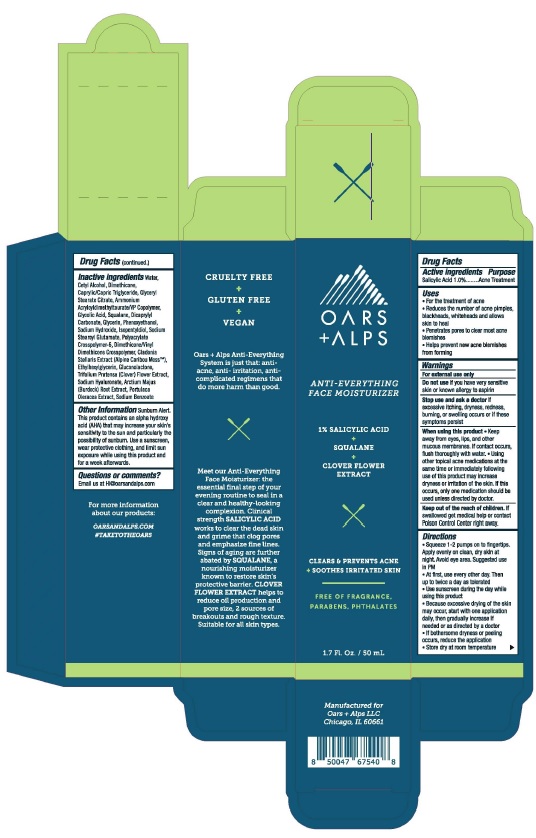 DRUG LABEL: Anti-Everything Face Moisturizer
NDC: 54111-181 | Form: LOTION
Manufacturer: Bentley Laboratories, LLC
Category: otc | Type: HUMAN OTC DRUG LABEL
Date: 20240805

ACTIVE INGREDIENTS: Salicylic Acid 1.0 g/100 mL
INACTIVE INGREDIENTS: WATER; CETYL ALCOHOL; DIMETHICONE; MEDIUM-CHAIN TRIGLYCERIDES; GLYCERYL STEARATE CITRATE; AMMONIUM ACRYLOYLDIMETHYLTAURATE/VP COPOLYMER; SQUALANE; DICAPRYLYL CARBONATE; GLYCERIN; PHENOXYETHANOL; SODIUM HYDROXIDE; ISOPENTYLDIOL; SODIUM STEAROYL GLUTAMATE; AMMONIUM ACRYLOYLDIMETHYLTAURATE, DIMETHYLACRYLAMIDE, LAURYL METHACRYLATE AND LAURETH-4 METHACRYLATE COPOLYMER, TRIMETHYLOLPROPANE TRIACRYLATE CROSSLINKED (45000 MPA.S); DIMETHICONE/VINYL DIMETHICONE CROSSPOLYMER (SOFT PARTICLE); CLADONIA RANGIFERINA WHOLE; ETHYLHEXYLGLYCERIN; GLUCONOLACTONE; TRIFOLIUM PRATENSE FLOWER; HYALURONATE SODIUM; ARCTIUM LAPPA ROOT; PORTULACA OLERACEA LEAF; SODIUM BENZOATE

Oars + Alps Anti-Everything Face Moisturizer

Drug Facts

Active Ingredients

Salicylic Acid 1.0%

Purpose

Acne Treatment

Uses
• For the treatment of acne
• Reduces the number of acne pimples,
blackheads, whiteheads and allows
skin to heal
• Penetrates pores to clear most acne
blemishes
• Helps prevent new acne blemishes
from formlng

Warnings
For external use only

Do not use if you have very sensitive
skin or known allergy to aspirin

Slop use and ask a doctor if
excessive itching, dryness, redness,
burning, or swelling occurs or if these
symptoms persist

When using this product • Keep
away from eyes, lips, and other
mucous membranes. If contact occurs,
flush thoroughly with water.• Using
other topical acne medications at the
same time or immediately following
use of this product may increase
dryness or irritation of the skin. If this
occurs, only one medication should be
used unless directed by doctor.

Keep out of the reach of children. If
swallowed get medical help or contact
Poison Control Center right away.

Directions
• Squeeze 1-2 pumps on to fingertips.
Apply evenly on clean, dry skin at
night. Avoid eye area. Suggested use
in PM.
• At first, use every other day. Then
up to twice a day as tolerated
• Use sunscreen during the day while
using this product
• Because excessive drying of the skin
may occur, start with one application
daily, then gradually increase if needed
or as directed by a doctor.
• If bothersome dryness or peeling
occurs, reduce the application.
• Store dry at room temperature

Inactive ingredients Water,
Cetyl Alcohol, Dimethicone,
Caprylic/Capric Triglyceride, Glyceryl
Stearate Citrate, Ammonium
Acryloyldimethyltaurate/VP Copolymer,
Glycolic Acid, Squalane, Dicaprylyl
Carbonate, Glycerin, Phenoxyethanol,
Sodium Hydroxide, Isopentyldiol, Sodium
Stearoyl Glutamate, Polyacrylate
Crosspolymer-6, Dimethicone/Vinyl
Dimethicone Crosspolymer, Cladonia
Stellaris Extract (Alpine Caribou Moss™),
Ethylhexylglycerin, Gluconolactone,
Trifolium Pratense (Clover) Flower Extract,
Sodium Hyaluronate, Arctium Majus
(Burdock) Root Extract, Portulaca
Oleracea Extract, Sodium Benzoate

Other Information Sunburn Alert.
This product contains an alpha hydroxy
acid (AHA) that may increase your skin's
sensitivity to the sun and particularly the
possibility of sunburn. Use a sunscreen,
wear protective clothing, and limit sun
exposure while using this product and
for a week afterwards.

Questions or comments?

Email us at HI@oarsandalps.com

Product Packaging: OARS + ALPS ANTI-EVERYTHING FACE MOISTURIZER

OARS + ALPS

ANTI-EVERYTHING

FACE MOISTURIZER

1% SALICYLIC ACID

1.7 Fl. Oz. / 50 mL

Manufactured for

Oars + Alps LLC

Chicago, IL 60661

res 080624